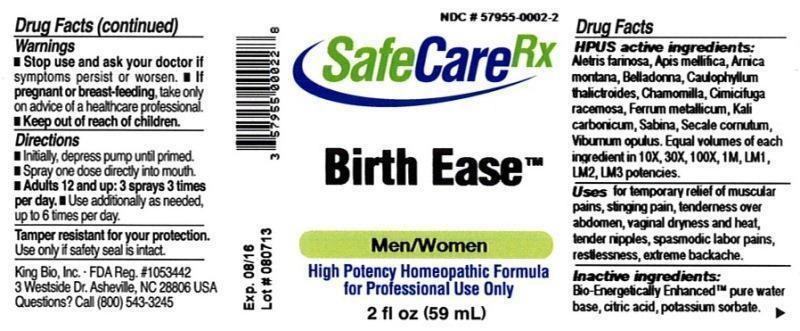 DRUG LABEL: Birth Ease
NDC: 57955-0002 | Form: LIQUID
Manufacturer: King Bio Inc.
Category: homeopathic | Type: HUMAN OTC DRUG LABEL
Date: 20140417

ACTIVE INGREDIENTS: ALETRIS FARINOSA ROOT 10 [hp_X]/59 mL; APIS MELLIFERA 10 [hp_X]/59 mL; ARNICA MONTANA 10 [hp_X]/59 mL; ATROPA BELLADONNA 10 [hp_X]/59 mL; CAULOPHYLLUM THALICTROIDES ROOT 10 [hp_X]/59 mL; MATRICARIA RECUTITA 10 [hp_X]/59 mL; BLACK COHOSH 10 [hp_X]/59 mL; IRON 10 [hp_X]/59 mL; POTASSIUM CARBONATE 10 [hp_X]/59 mL; JUNIPERUS SABINA LEAFY TWIG 10 [hp_X]/59 mL; CLAVICEPS PURPUREA SCLEROTIUM 10 [hp_X]/59 mL; VIBURNUM OPULUS BARK 10 [hp_X]/59 mL
INACTIVE INGREDIENTS: WATER; CITRIC ACID MONOHYDRATE; POTASSIUM SORBATE

Birth Ease™

ACTIVE INGREDIENT

Drug Facts__________________________________________________________________________________________________________

HPUS active ingredients: Aletrus farinosa, Apis mellifica, Arnica montana, Belladonna, Caulophyllum thalictroides, Chamomilla, Cimicifuga racemosa, Ferrum metallicum, Kali carbonicum, Sabina, Secale cornutum, Viburnum opulus. Equal volumes of each ingredient in 10X, 30X, 100X, 1M, LM1, LM2, LM3 potencies.

INDICATIONS AND USAGE

Uses for temporary relief of: Muscular pains, stinging pain, tenderness over abdomen, vaginal dryness and heat, tender nipples, spasmodic labor pains, restlessness, extreme backache.

Inactive Ingredients:

Bio-Energetically Enhanced™ pure water, citric acid and potassium sorbate.

Warnings

- Stop use and ask your doctor if symptoms persist or worsen.
- If pregnant or breast-feeding, take only on advice of a healthcare professional.

- Keep out of reach of children.

Directions

- Initially, depress pump until primed.
- Spray one dose directly into mouth.
- Adults: 12 and up: 3 sprays 3 times per day.
- Use additionally as needed, up to 6 times per day.

OTHER SAFETY INFORMATION

Tamper resistant for your protection. Use only if safety seal is intact.

PURPOSE

Uses for temporary relief of:

- muscular pains
- stinging pain
- tenderness over abdomen
- vaginal dryness and heat
- tender nipples
- spasmodic labor pains
- restlessness
- extreme backache